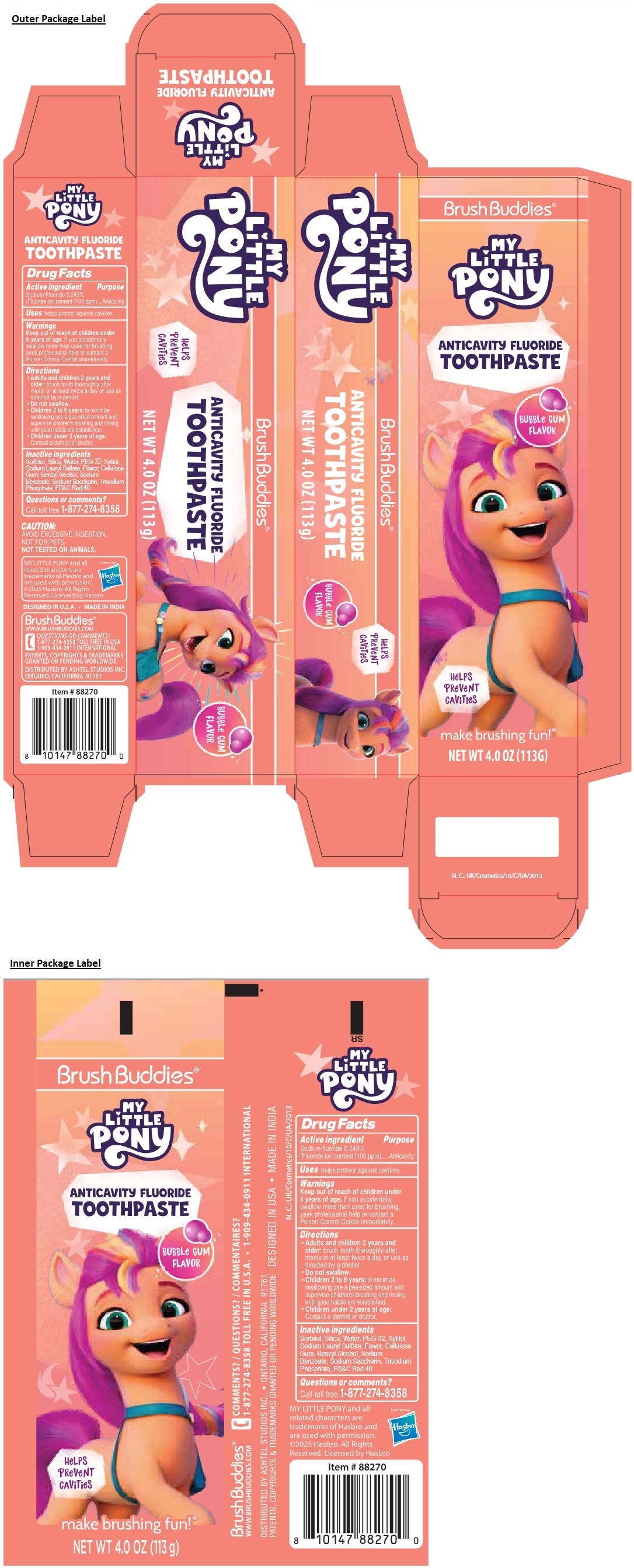 DRUG LABEL: Brush Buddies MY LITTLE PONY ANTICAVITY FLUORIDE
NDC: 70108-112 | Form: PASTE, DENTIFRICE
Manufacturer: Ashtel Studios, Inc.
Category: otc | Type: HUMAN OTC DRUG LABEL
Date: 20250129

ACTIVE INGREDIENTS: SODIUM FLUORIDE 0.243 g/100 g
INACTIVE INGREDIENTS: SORBITOL; SILICON DIOXIDE; WATER; POLYETHYLENE GLYCOL 1600; XYLITOL; SODIUM LAURYL SULFATE; CARBOXYMETHYLCELLULOSE SODIUM, UNSPECIFIED; BENZYL ALCOHOL; SODIUM BENZOATE; SACCHARIN SODIUM; SODIUM PHOSPHATE, TRIBASIC, ANHYDROUS; FD&C RED NO. 40

Brush Buddies® MY LITTLE PONY ANTICAVITY FLUORIDE TOOTHPASTE

Active ingredient

Sodium Fluoride 0.243%
(Fluoride ion content 1100 ppm)

Purpose

Anticavity

Uses

helps protect against cavities.

Warnings

Keep out of reach of children under 6 years of age. If you accidently swallow more than used for brushing, seek professional help or contact a Poison Control Center immediately.

Directions

- Adults and children 2 years and older: brush teeth thoroughly after meals or at least twice a day or use as directed by a dentist.
- Do not swallow.
- Children 2 to 6 years: to minimize swallowing use a pea-sized amount and supervise children's brushing and rinsing until good habits are established.
- Children under 2 years of age: Consult a dentist or doctor.

Inactive ingredients

Sorbitol, Silica, Water, PEG-32, Xylitol, Sodium Lauryl Sulfate, Flavor, Cellulose Gum, Benzyl Alcohol, Sodium Benzoate, Sodium Saccharin, Trisodium Phosphate, FD&C Red 40

Questions or comments?

Call toll free 1-877-274-8358

BrushBuddies®

BUBBLe GUM FLAVOR

HeLPS PReVeNT CAViTieS

make brushing fun!®

CAUTION:
AVOID EXCESSIVE INGESTION.
NOT FOR PETS.
NOT TESTED ON ANIMALS.

MY LITTLE PONY and all related characters are trademarks of Hasbro and are used with permission.
©2025 Hasbro. All Rights Reserved. Licensed by Hasbro

DESIGNED IN U.S.A. • MADE IN INDIA

WWW.BRUSHBUDDIES.COM
QUESTIONS OR COMMENTS?
1-909-434-0911 INTERNATIONAL

PATENTS, COPYRIGHTS & TRADEMARKS GRANTED OR PENDING WORLDWIDE

DISTRIBUTED BY ASHTEL STUDIOS INC.
ONTARIO, CALIFORNIA 91761